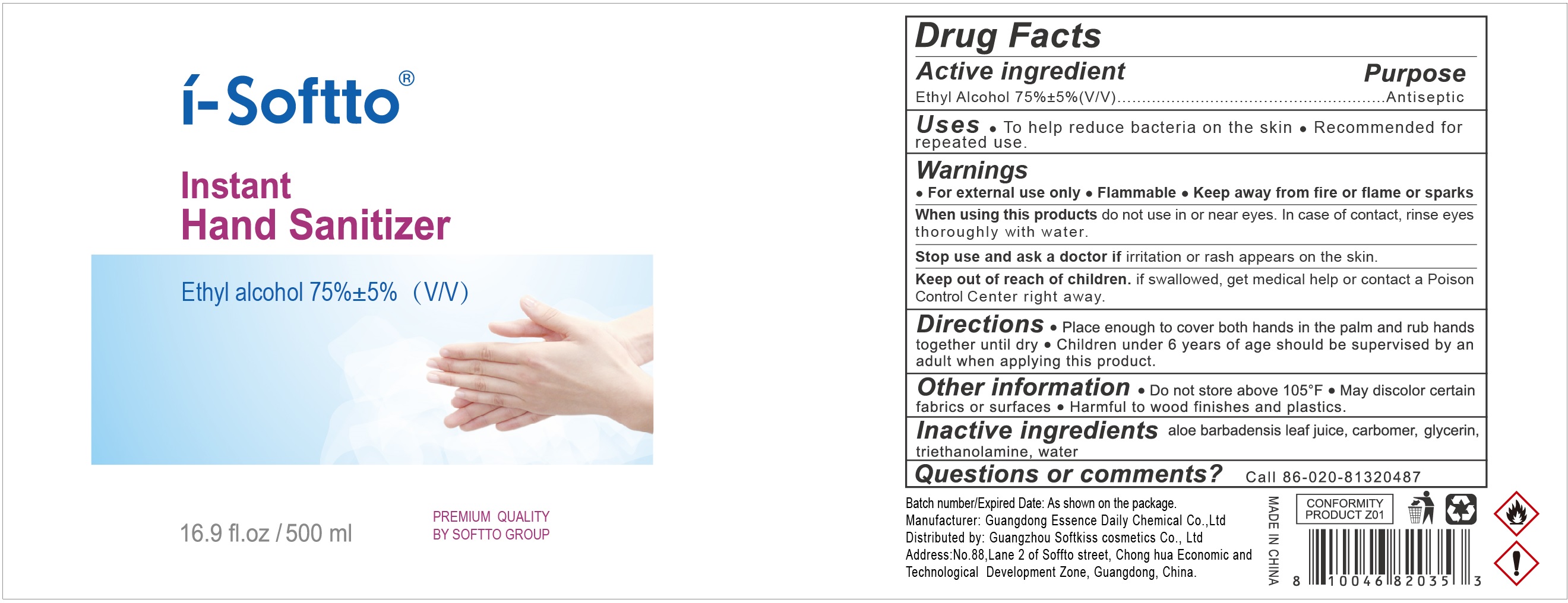 DRUG LABEL: I-Softto Instant hand Sanitizer
NDC: 73931-005 | Form: GEL
Manufacturer: Guangdong Essence Daily Chemical Co., Ltd
Category: otc | Type: HUMAN OTC DRUG LABEL
Date: 20200623

ACTIVE INGREDIENTS: ALCOHOL 75 mL/100 mL
INACTIVE INGREDIENTS: WATER; GLYCERIN; TROLAMINe; ALOE VERA LEAF

Active ingredient

Ethyl Alcohol 75% +/-5% (V/V)

Purpose

Antiseptic

Use

To help reduce bacteria on the skin and recomended for repeated use.

Warnings

For external use only.

Flammable,

Keep product away from fire or flame or sparks.

When using this product

do not use in or neay eyes, In case of contact, rinse eyes thoroughly with water.

Stop use and ask a doctor if

irritation or rash appears on the skin.

Keep out of reach of children.

If swallowed, get medical help or contact a Poison Control Center right away.

Directions

- Place enough to cover both hands in the palm, and rub hands together until dry
- Children under 6 years of age should be supervised bu an adult when appling this products.

Inactive ingredients

Water, Glycerin, Carbomer, Triethanolamine, Aloe Barbadensis Leaf Juice.

other information

- Do not store above 105 Fahrenheit.
- May discolor certain fabrics or surfaces.
- Harmful to wood finishes and plastics.